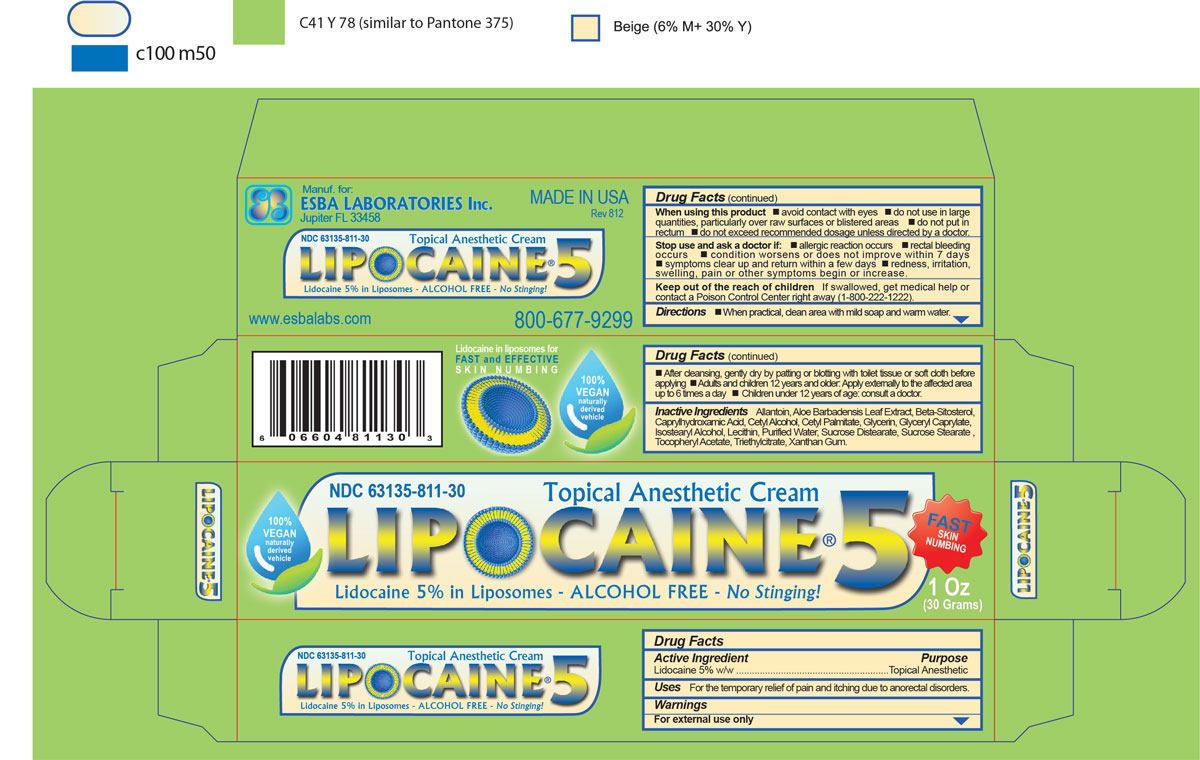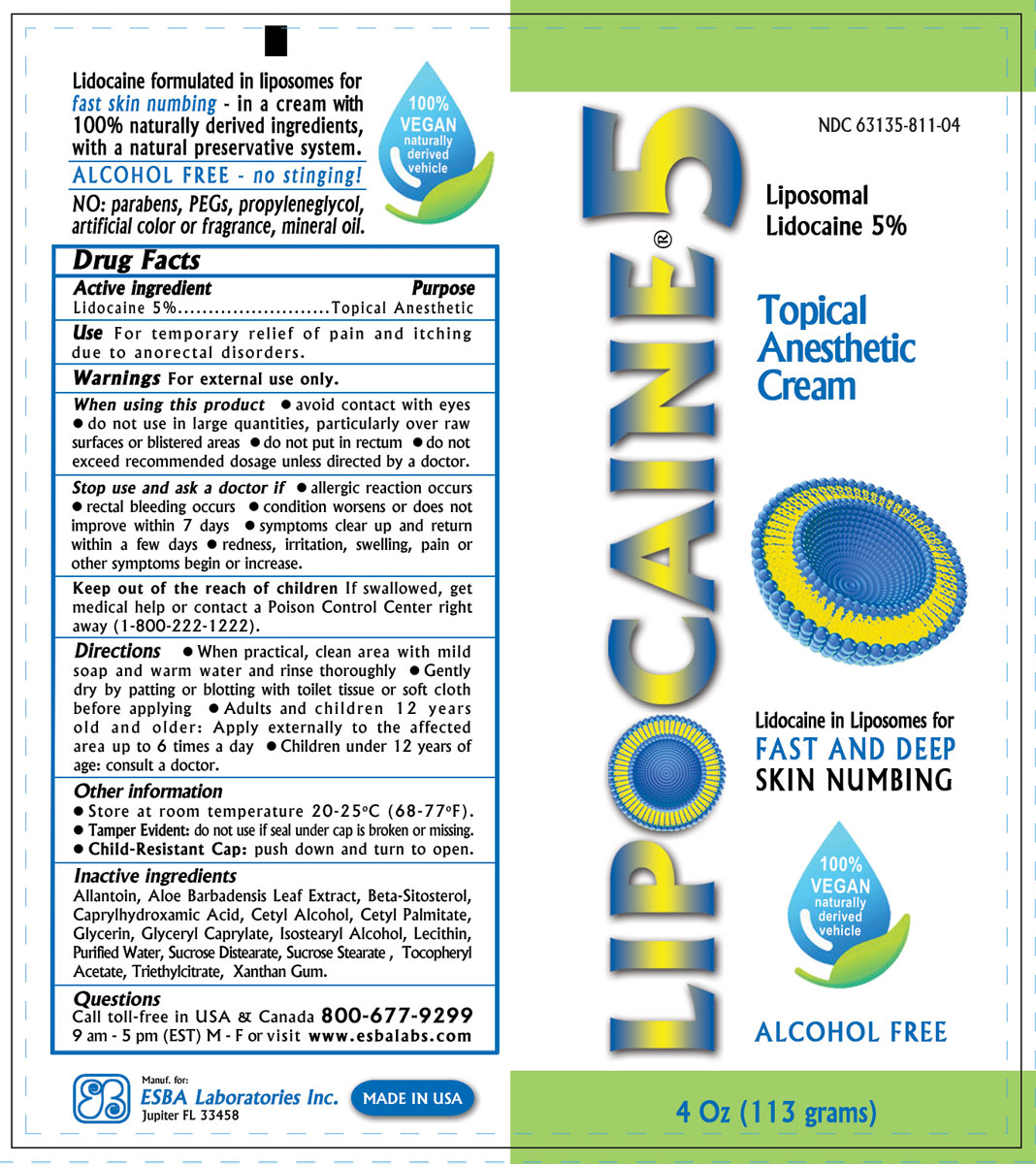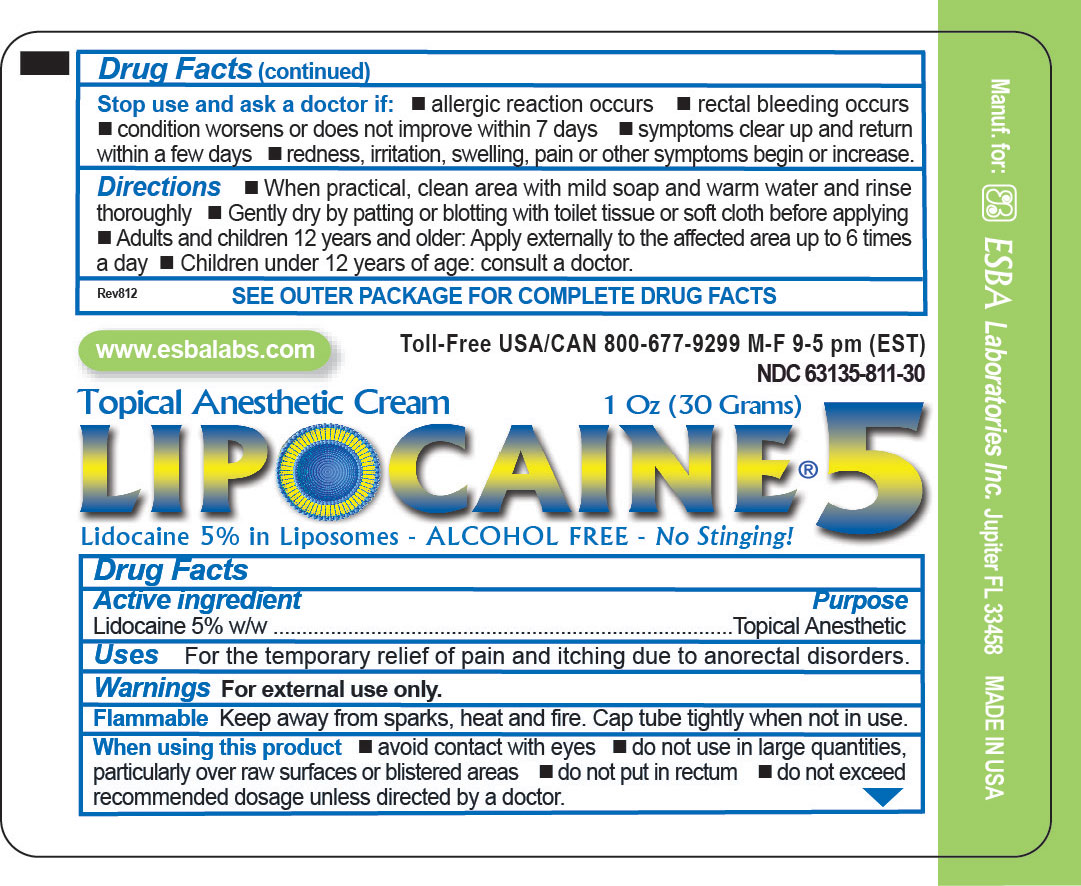 DRUG LABEL: LIPOCAINE 5
NDC: 63135-811 | Form: CREAM
Manufacturer: ESBA LABORATORIES INC.
Category: otc | Type: HUMAN OTC DRUG LABEL
Date: 20240919

ACTIVE INGREDIENTS: LIDOCAINE 5 g/100 g
INACTIVE INGREDIENTS: ALLANTOIN 0.01 g/100 g; XANTHAN GUM 1.5 g/100 g; SUCROSE DISTEARATE 2 g/100 g; .BETA.-SITOSTEROL 0.5 g/100 g; CAPRYLHYDROXAMIC ACID 0.12 g/100 g; GLYCERYL CAPRYLATE 0.6 g/100 g; GLYCERIN 0.48 g/100 g; CETYL PALMITATE 5 g/100 g; CETYL ALCOHOL 0.25 g/100 g; WATER 71.77 g/100 g; ISOSTEARYL ALCOHOL 0.25 g/100 g; LECITHIN, SUNFLOWER 0.01 g/100 g; TRIETHYL CITRATE 10 g/100 g; SUCROSE STEARATE 2 g/100 g; .ALPHA.-TOCOPHEROL ACETATE, DL- 0.5 g/100 g; ALOE VERA LEAF 0.01 g/100 g

LIPOCAINE 5

Active ingredient:

Lidocaine 5%

Purpose

Topical Anesthetic

Use

For temporary relief of pain and itching due to anorectal disorders.

Warnings

For external use only.

When using this product:

- avoid contact with eyes
- do not use in large quantities, particularly over raw surfaces or blistered areas
- do not put in rectum
- do not exceed recommended dosage unless directed by a doctor.

Stop use and ask a doctor if:

- allergic reaction occurs
- rectal bleeding occurs
- condition worsens or does not improve within 7 days
- symptoms clear up and return within a few days
- redness, irritation, swelling, pain or other symptoms begin or increase.

Keep out of the reach of children:

If swallowed, get medical help or contact a Poison Control Center right away (1-800-222-1222).

Directions:

- When practical, clean area with mild soap and warm water and rinse thoroughly
- Gently dry by patting or blotting with toilet tissue or soft cloth before applying
- Adults and children 12 years old and older: Apply externally to the affected area up to 6 times a day
- Children under 12 years of age: consult a doctor.

Other information:

- Store at room temperature 20-25oC (68-77oF).
- Child-Resistant Cap: push down and turn to open
- Available in 1 Oz (30 g) and 4 Oz (113 g) tubes

Inactive ingredients:

Allantoin, Aloe Barbadensis Leaf Extract, Beta-Sitosterol, Caprylhydroxamic Acid, Cetyl Alcohol, Cetyl Palmitate, Glycerin, Glyceryl Caprylate, Isostearyl Alcohol, Lecithin, Purified Water, Sucrose Distearate, Sucrose Stearate , Tocopheryl Acetate, Triethylcitrate, Xanthan Gum.

Questions

Call toll-free in USA & Canada 800-677-9299 9 am - 5 pm (EST) M - F or visit www.esbalabs.com

Label on tube and outer carton

Lipocaine 5 tube 113 grams label

Lipocaine 5 tube 30 grams label

Outer carton of Lipocaine 5 - 30 g tube